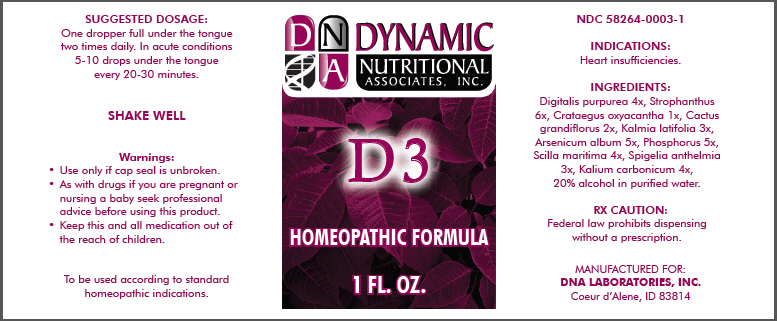 DRUG LABEL: D3
NDC: 58264-0003 | Form: SOLUTION
Manufacturer: DNA Labs, Inc.
Category: homeopathic | Type: HUMAN OTC DRUG LABEL
Date: 20180201

ACTIVE INGREDIENTS: DIGITALIS PURPUREA WHOLE 4 [hp_X]/1 mL; STROPHANTHUS HISPIDUS WHOLE 6 [hp_X]/1 mL; CRATAEGUS MEXICANA WHOLE 1 [hp_X]/1 mL; SELENICEREUS GRANDIFLORUS WHOLE 2 [hp_X]/1 mL; KALMIA LATIFOLIA WHOLE 3 [hp_X]/1 mL; ARSENIC TRIOXIDE 5 [hp_X]/1 mL; PHOSPHORUS 5 [hp_X]/1 mL; DRIMIA MARITIMA WHOLE 4 [hp_X]/1 mL; SPIGELIA ANTHELMIA 3 [hp_X]/1 mL; POTASSIUM CARBONATE 4 [hp_X]/1 mL
INACTIVE INGREDIENTS: ALCOHOL; WATER

D3

NDC 58264-0003-1

INDICATIONS

PURPOSE

Heart insufficiencies.

ACTIVE INGREDIENT

INGREDIENTS

Digitalis purpurea 4x, Strophanthus 6x, Crataegus oxyacantha 1x, Cactus grandiflorus 2x, Kalmia latifolia 3x, Arsenicum album 5x, Phosphorus 5x, Scilla maritima 4x, Spigelia anthelmia 3x, Kalium carbonicum 4x, 20% alcohol in purified water.

RX CAUTION

Federal law prohibits dispensing without a prescription.

SUGGESTED DOSAGE

One dropper full under the tongue two times daily. In acute conditions 5-10 drops under the tongue every 20-30 minutes.

STORAGE AND HANDLING

SHAKE WELL

Warnings

- Use only if cap seal is unbroken.

PREGNANCY OR BREAST FEEDING

- As with drugs if you are pregnant or nursing a baby seek professional advice before using this product.

KEEP OUT OF REACH OF CHILDREN

- Keep this and all medication out of the reach of children.

To be used according to standard homeopathic indications.

PRINCIPAL DISPLAY PANEL - 1 FL. OZ. Bottle Label

DYNAMIC
NUTRITIONAL
ASSOCIATES, INC.

D 3

HOMEOPATHIC FORMULA

1 FL. OZ.